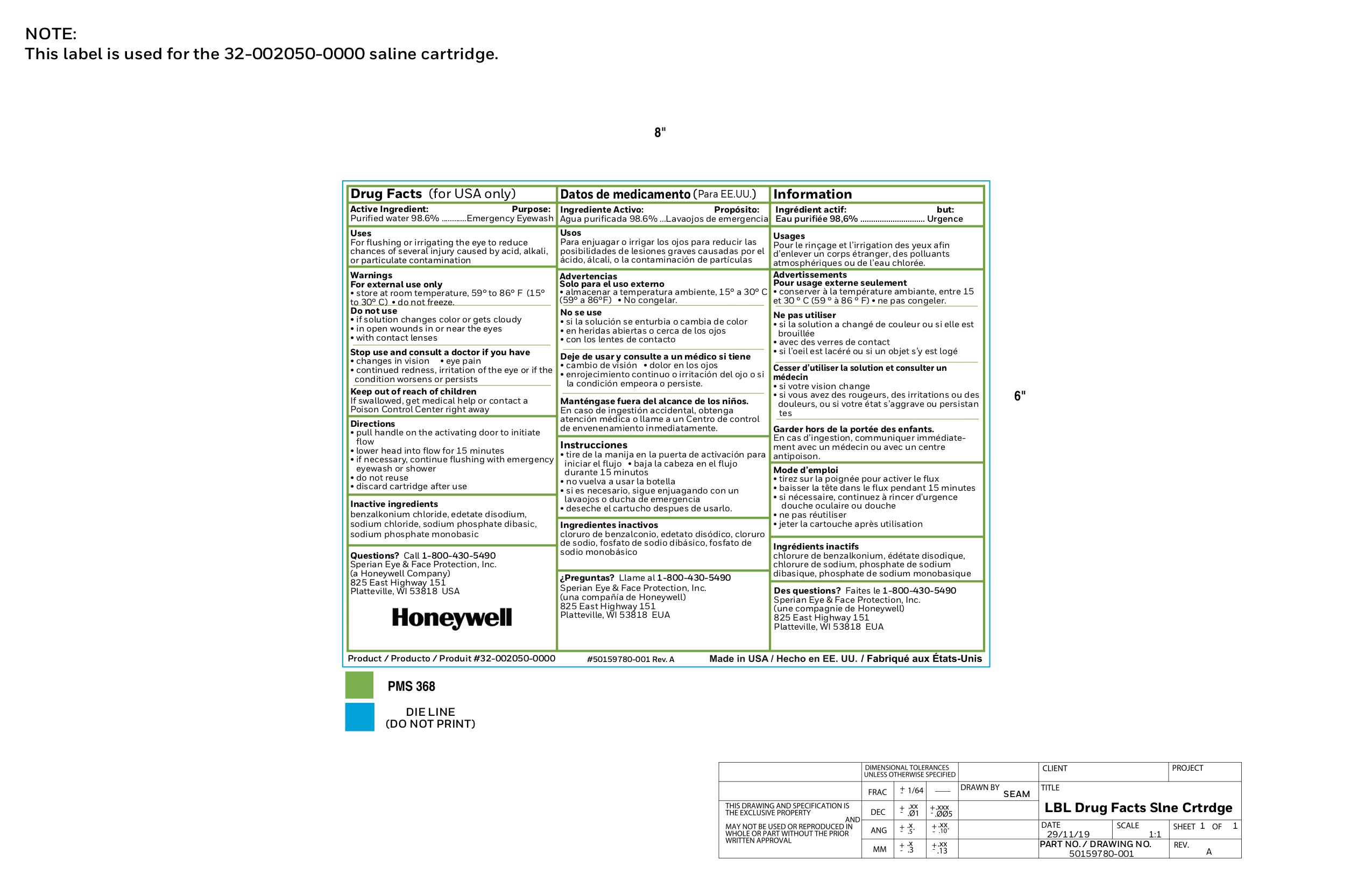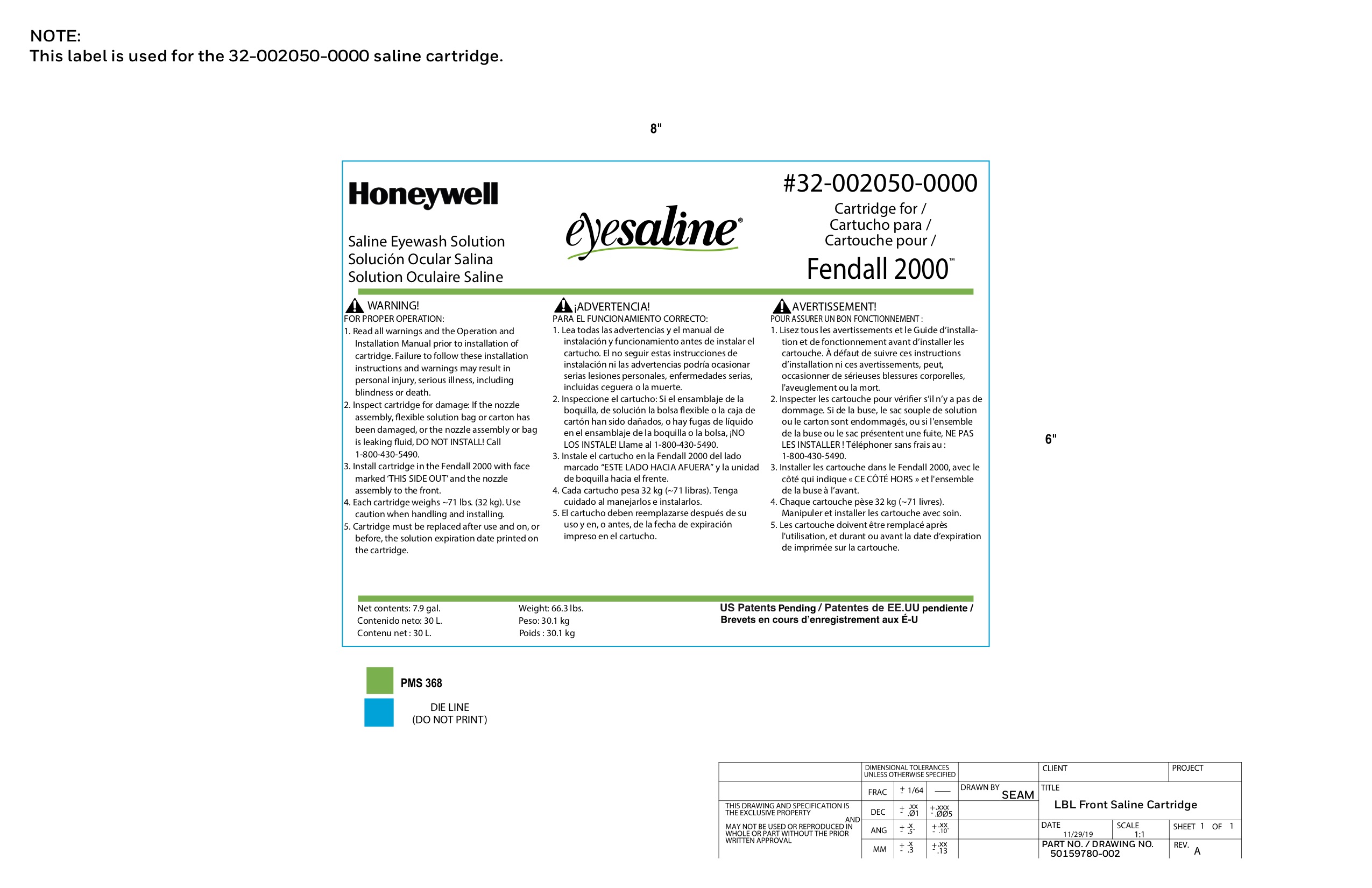 DRUG LABEL: Fendall 2000 Pure Flow
NDC: 0498-0631 | Form: LIQUID
Manufacturer: Honeywell Safety Products USA, Inc.
Category: otc | Type: HUMAN OTC DRUG LABEL
Date: 20240106

ACTIVE INGREDIENTS: WATER 98.6 L/100 L
INACTIVE INGREDIENTS: EDETATE DISODIUM; BENZALKONIUM CHLORIDE; SODIUM CHLORIDE; SODIUM PHOSPHATE, MONOBASIC, MONOHYDRATE; SODIUM PHOSPHATE, DIBASIC

0498-0631: Fendall 2000 Pure flow

Active ingredient

Purified Water 98.6%

Purpose

Emergency Eyewash

Uses

For flushing or irrigating the eye to reduce chances of severe injury caused by acid, alkali, or particulate contamination

Warnings

For external use only

- store at room temperature, 59o to 86oF (15o to 30oC)
- do not freeze

Do not use

- if solution changes color or gets cloudy
- in open wounds in or near the eyes
- with contact lenses

Stop use and ask a doctor if you have

- changes in vision
- eye pain
- continued redness, irritation of the eye or if the condition worsens or persists

Keep out of reach of children

If swallowed, get medical help or contact a Poison Control Center right away

Directions

- pull handle on the activating door to initiate flow
- lower head into flow for 15 minutes
- if necessary, continue flushing with emergency eyewash or shower
- do not reuse
- discard cartridge after use

Inactive ingredients

benzlkonium chloride, edetate disodium, sodium chloride, sodium phosphate dibasic, sodium phosphate monobasic

Questions?

Call 1-800-430-5490

Sperian Eye & Face Protecton, Inc.

(a Honeywell Company)

825 East Highway 151

Platteville, WI 53818 USA